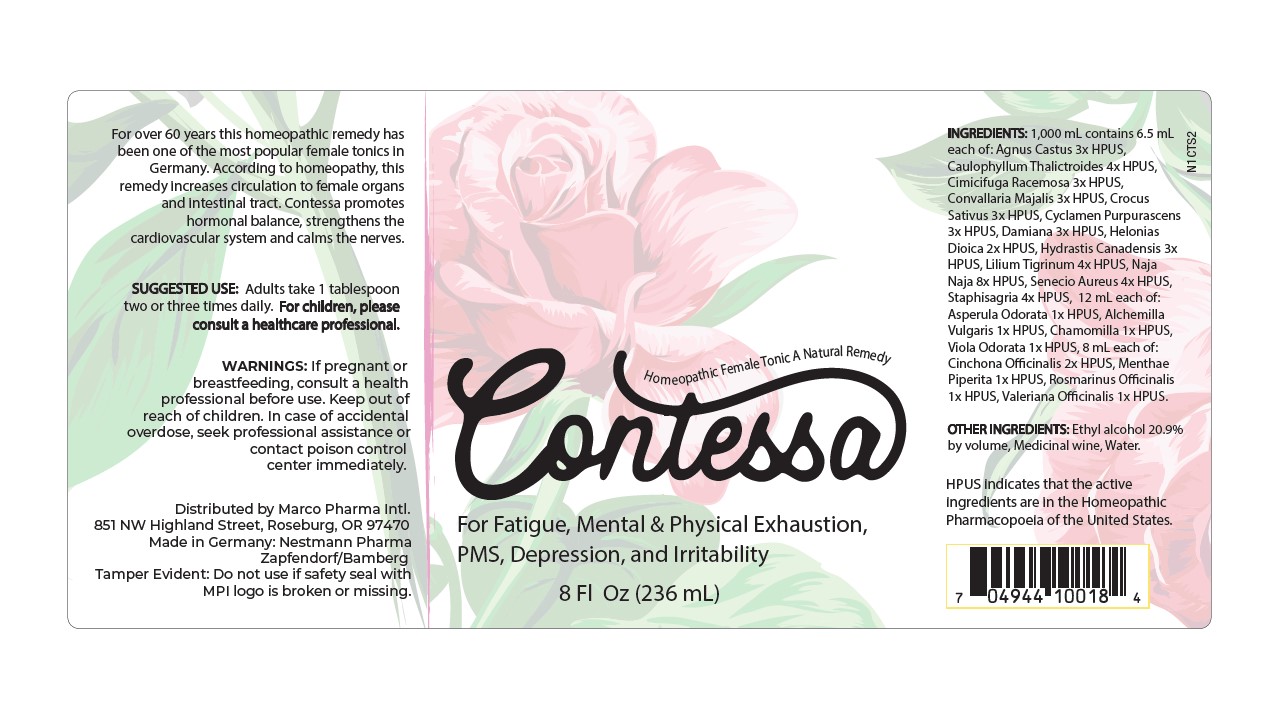 DRUG LABEL: Contessa
NDC: 60986-1014 | Form: LIQUID
Manufacturer: Marco Pharma International LLC.
Category: homeopathic | Type: HUMAN OTC DRUG LABEL
Date: 20260126

ACTIVE INGREDIENTS: ALCHEMILLA XANTHOCHLORA FLOWERING TOP 1 [hp_X]/100 mL; GALIUM ODORATUM 1 [hp_X]/100 mL; MATRICARIA RECUTITA 1 [hp_X]/100 mL; VIOLA ODORATA 1 [hp_X]/100 mL; CINCHONA OFFICINALIS BARK 2 [hp_X]/100 mL; MENTHA PIPERITA 1 [hp_X]/100 mL; ROSMARINUS OFFICINALIS FLOWERING TOP 1 [hp_X]/100 mL; VALERIAN 1 [hp_X]/100 mL; CHAMAELIRIUM LUTEUM ROOT 2 [hp_X]/100 mL; CHASTE TREE 3 [hp_X]/100 mL; AMBERGRIS 3 [hp_X]/100 mL; BLACK COHOSH 3 [hp_X]/100 mL; CONVALLARIA MAJALIS 3 [hp_X]/100 mL; SAFFRON 3 [hp_X]/100 mL; CYCLAMEN PURPURASCENS TUBER 3 [hp_X]/100 mL; TURNERA DIFFUSA LEAFY TWIG 3 [hp_X]/100 mL; GOLDENSEAL 3 [hp_X]/100 mL; CAULOPHYLLUM THALICTROIDES ROOT 4 [hp_X]/100 mL; LILIUM LANCIFOLIUM FLOWERING TOP 4 [hp_X]/100 mL; PACKERA AUREA 4 [hp_X]/100 mL; DELPHINIUM STAPHISAGRIA SEED 4 [hp_X]/100 mL; NAJA NAJA VENOM 8 [hp_X]/100 mL
INACTIVE INGREDIENTS: ALCOHOL; WATER

Drug Facts

Active Ingredients

Alchemilla Vulgaris 1x

Asperula Odorata 1xHPUS

Chamomilla 1xHPUS

Viola Odorata 1xHPUS

Cinchona Officinalis 2x

Mentha Piperita 1xHPUS

Rosmarinus Officinalis 1xHPUS

Valeriana Officinalis 1xHPUS

Helonias Dioica 2xHPUS

Agnus Castus 3XHPUS

Ambra Grisea 3xHPUS

Cimicifuga Racemosa 3xHPUS

Convalleria Majalis 3xHPUS

Crocus Sativus 3xHPUS

Cyclamen Europaeum 3xHPUS

Damiana 3xHPUS

Hydrastis Canadensis 3xHPUS

Caulophyllum Thalictroides 4xHPUS

Lilium Tigrinum 4xHPUS

Senecio Aureus 4xHPUS

Staphysagria 4xHPUS

Naja Tripudians 8xHPUS

The letters HPUS indicates that the components in this product are officially monographed in the Homeopathic Pharmacopoeia of United Sates.

Purpose

For fatigue, mental and physical exhaustion, PMS, depression and irritability.

Keep out of reach of children.

Suggested use

Adults take 1 tablespoon two to three times daily. Children 12 to 18 years of age take 1 teaspoon two to three times daily. Not intended for children under 12 years of age.

Warnings

If pregnant or breast-feeding, consult a health professional before use. In case of accidental overdose, seek professional assistance or contact a poison control center immediately.

DOSAGE AND ADMINISTRATION

(Read Suggested Use Section)

Inactive Ingredients

Ethyl Alcohol (20.9% by vol.) and Water